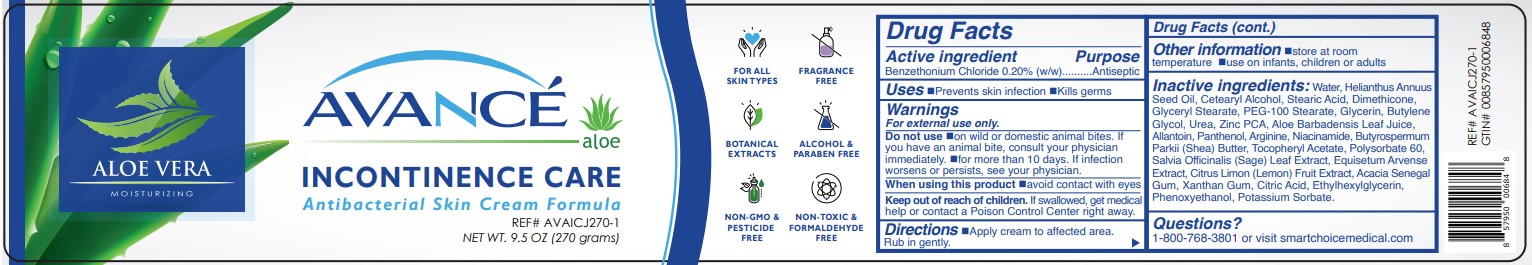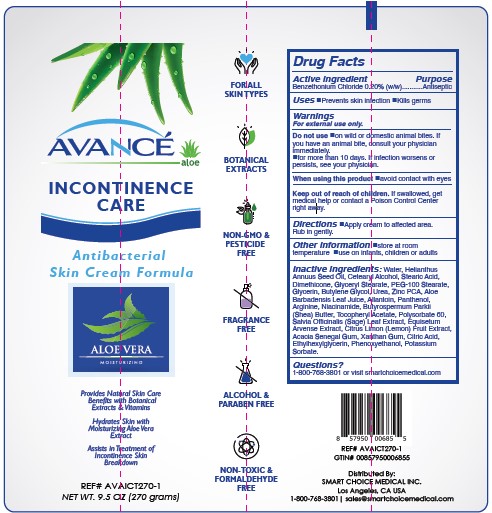 DRUG LABEL: AVANCE INCONTINENCE CARE
NDC: 70936-111 | Form: CREAM
Manufacturer: SMART CHOICE MEDICAL INC.
Category: otc | Type: HUMAN OTC DRUG LABEL
Date: 20260112

ACTIVE INGREDIENTS: BENZETHONIUM CHLORIDE 0.2 g/100 g
INACTIVE INGREDIENTS: .ALPHA.-TOCOPHEROL ACETATE; CETOSTEARYL ALCOHOL; STEARIC ACID; DIMETHICONE; GLYCERYL MONOSTEARATE; XANTHAN GUM; PHENOXYETHANOL; ETHYLHEXYLGLYCERIN; WATER; ALOE VERA LEAF; PANTHENOL; SHEA BUTTER; GLYCERIN; PEG-100 STEARATE; BUTYLENE GLYCOL; UREA; POLYSORBATE 60; ZINC PIDOLATE; ALLANTOIN; ARGININE; SUNFLOWER OIL; POTASSIUM SORBATE; NIACINAMIDE; SAGE; LEMON JUICE; ANHYDROUS CITRIC ACID; ACACIA; EQUISETUM ARVENSE WHOLE

SMART CHOICE MEDICAL - AVANCE INCONTINENCE CARE (70936-111)

ACTIVE INGREDIENT:

BENZETHONIUM CHLORIDE 0.20% (W/W)

PURPOSE

ANTISEPTIC

USES

- PREVENTS SKIN INFECTION
- KILLS GERMS

WARNINGS:

- FOR EXTERNAL ONLY

DO NOT USE:

- ON WILD OR DOMESTIC ANIMAL BITES. IF YOU HAVE AN ANIMAL BITE, CONSULT YOUR PHYSICIAN IMMEDIATELY.
- ON INFECTIONS
- FOR MORE THAN 10 DAYS. IF INFECTION WORSENS OR PERSISTS, SEE YOUR PHYSICIAN.

WHEN USING THIS PRODUCT:

- AVOID CONTACT WITH EYES

KEEP OUT OF REACH OF CHILDREN

KEEP OUT OF REACH OF CHILDERN. IF SWALLOWED GET MEDICAL HELP OR CONTACT A POISON CONTROL CENTER RIGHT AWAY

DIRECTIONS

- APPPLY CREAM TO AFFECTED AREA. RUB IN GENTLY.

OTHER INFORMATION

- STORE AT ROOM TEMPERATURE
- USE ON INFANTS, CHILDREN OR ADULTS

INACTIVE INGREDIENTS

Water, Helianthus Annuus Seed Oil, Cetearyl Alcohol, Stearic Acid, Dimethicone, Glyceryl Stearate, PEG-100 Stearate, Glycerin, Butylene Glycol, Urea, Zinc PCA, Aloe Barbadensis Leaf Juice, Allantoin, Panthenol, Arginine, Niacinamide, Butyrospermum
Parkii (Shea) Butter, Tocopheryl Acetate, Polysorbate 60, Salvia Officinalis (Sage) Leaf Extract, Equisetum Arvense Extract, Citrus Limon (Lemon) Fruit Extract, Acacia Senegal Gum, Xanthan Gum, Citric Acid, Ethylhexylglycerin, Phenoxyethanol, Potassium Sorbate.